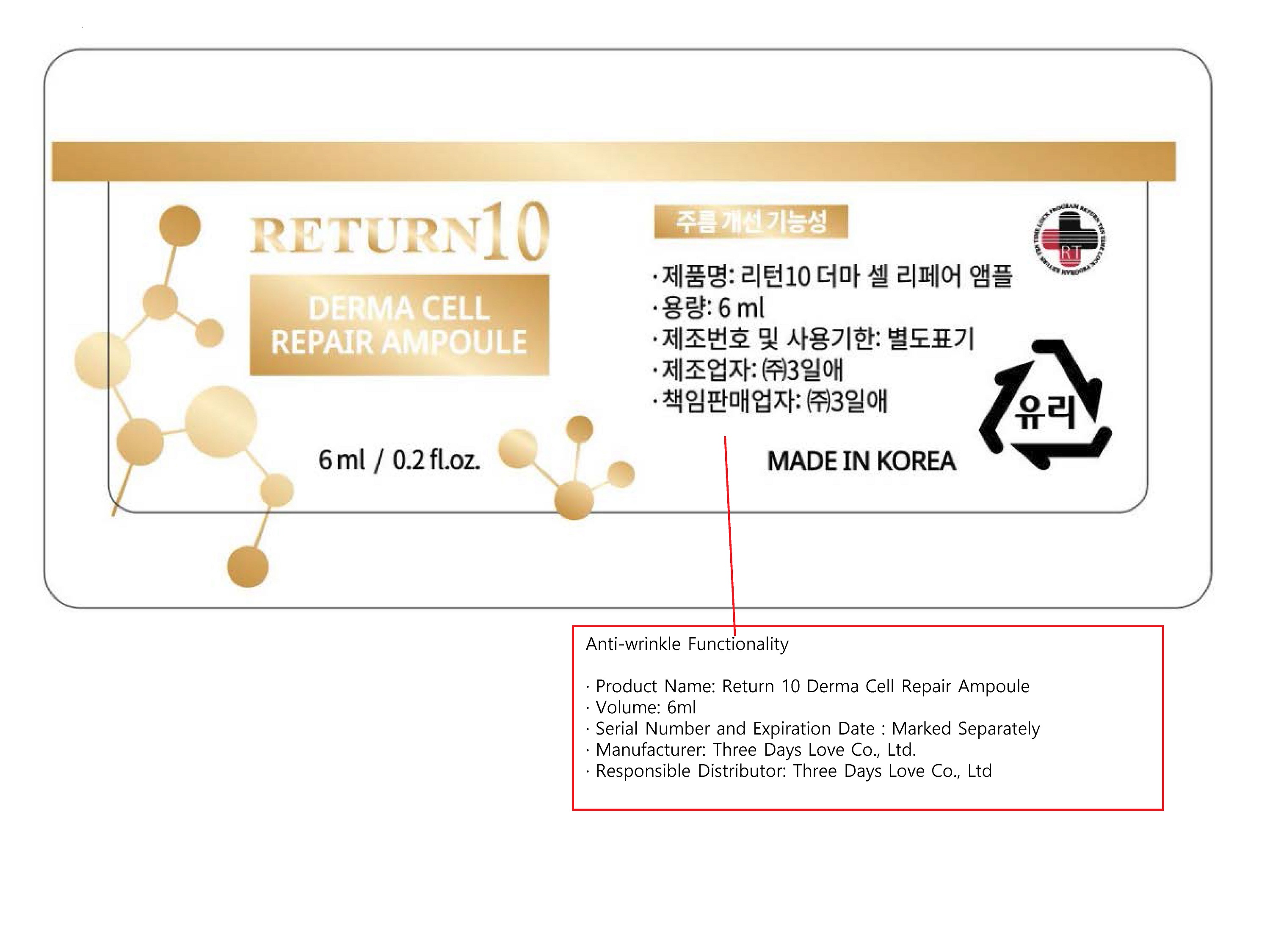 DRUG LABEL: RETURN10 Derma Cell Repair Ampoule
NDC: 72368-0008 | Form: LIQUID
Manufacturer: Threedayslove Co., Ltd.
Category: otc | Type: HUMAN OTC DRUG LABEL
Date: 20200104

ACTIVE INGREDIENTS: ADENOSINE 0.04 g/100 mL; NIACINAMIDE 3 g/100 mL
INACTIVE INGREDIENTS: WATER; BUTYLENE GLYCOL

Drug Facts

ACTIVE INGREDIENT

niacinamide, Adenosine

INACTIVE INGREDIENT

Water, Glycerin, Snail Secretion Filtrate, Portulaca Oleracea Extract, CentellaAsiaticaExtract ,Galactomyces Ferment Filtrate, Niacinamide, Camellia Sinensis Leaf Extract, Butylene Glycol, Betaine, Trehalose, Argania Spinosa Kernel Oil , Olea Europaea (Olive) Fruit Oil, Carbomer, Arbutin, 1,2-Hexanediol,

CaprylylGlycol ,Bis-PEG-18 Methyl Ether Dimethyl Silane, Illicium Verum (Anise) Fruit Extract , Sodium Hyaluronate, PEG-6 Methyl Ether, Adenosine, Aloe Barbadensis Leaf Extract, Propolis Extract, Glycyrrhiza Uralensis (Licorice) Root Extract , Schisandra Chinensis Fruit Extract , CoptisChinensis Root Extract,

Honey Extract, Lecithin, PEG-40 Hydrogenated Castor Oil, Tromethamine, CetearylOlivate, SorbitanOlivate, Phaseolus Radiatus Extract, Tranexamic Acid, Polyglutamic Acid, Panthenol, LeontopodiumAlpinum Callus Culture Extract, Disodium EDTA , Sodium Ascorbyl Phosphate, (-)-alpha-bisabolol, PPG-26-Buteth-26, rh-Oligopeptide-1, Polysorbate 20, Dipropylene Glycol, Dipotassium Glycyrrhizate, Alcohol, Copper Tripeptide-1, Acetyl HexaPeptide-8, Ethylhexylglycerin, Palmitoyl Tetrapeptide-7

PURPOSE

anti-wrinkle fucntionality

keep out of reach of the children

INDICATIONS AND USAGE

STEP1. Please wash your face cleanly.

STEP2. Spray the peptide effector ll mist on your face.

STEP3. After using mist in the morning and evening, take an appropriate amount of this product and put it on smoothly and absorb well according to skin texture.

STEP4. Massage the product gently into your skin using your fingers.

WARNINGS

Warning: 1. Do not use if you have any of following problems during use: ① Rash, red spots, swelling, irritation ② If the application site has any of the above problems due to direct sunlight

2. Precautions for storage and handling ① Close the cap after use ② Keep out of reach of children ③ Do not store under high or low temperature and direct sunlight.

If you continue to use the product, the symptoms may worsen. Stop use and ask a doctor if abnormality occurs.

DOSAGE AND ADMINISTRATION

for external use only